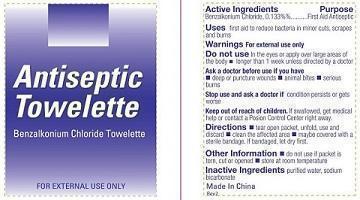 DRUG LABEL: ANTISEPTIC TOWELETTE
NDC: 42961-500 | Form: SWAB
Manufacturer: Cintas Corp.
Category: otc | Type: HUMAN OTC DRUG LABEL
Date: 20131219

ACTIVE INGREDIENTS: BENZALKONIUM CHLORIDE 0.13 g/100 g
INACTIVE INGREDIENTS: WATER; SODIUM BICARBONATE

ANTISEPTIC TOWELETTE

Active ingredient

Benzalkonium Chloride, 0.13%

Purpose

First Aid Antiseptic

USES

First aid to reduce bacteria in minor cuts, scrapes and burns

Warnings

Warnings for external use only

Do not use

- in the eyes or apply over large areas of the body
- longer than 1 week unless directed by a doctor.

Ask a doctore before use if you have

- deep or puncture wounds
- animal bites
- serious burns

Stop use and consult a doctor

if the condition persists or gets worse.

Keep out of reach of Children

If Swallowed, get medical help or contact a Poision Control Center right away

Directions

- tear open packet, unfold, use and discard
- clean the affected area
- maybe covered with a sterile bandage. If bandaged, let dry first

Inactive ingredients

purified water, sodium bicarbonate

Other Information

- do not use if packet is torn, cut or opened
- store at room temperature